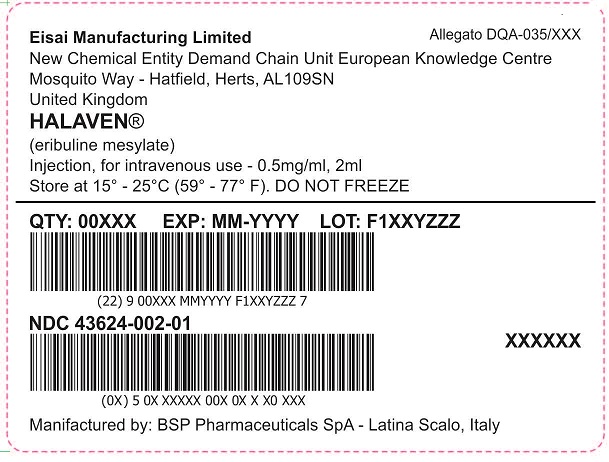 DRUG LABEL: Halaven
NDC: 43624-002 | Form: INJECTION
Manufacturer: BSP Pharmaceuticals SpA
Category: prescription | Type: HUMAN PRESCRIPTION DRUG LABEL
Date: 20251224

ACTIVE INGREDIENTS: ERIBULIN MESYLATE 0.5 mg/1 mL
INACTIVE INGREDIENTS: ALCOHOL; WATER

HALAVEN® (eribulin mesylate) injection 0.5 mg/mL

Halaven®

(eribulin mesylate) Injection, for intravenous use
1 mg/2 mL (0.5 mg/mL)

PRINCIPAL DISPLAY PANEL - SHIPPER LABEL

Eisai Manufacturing Limited

Allegato DQA-035/XXXX

New Chemical Entity Demand Chain Unit European Knowledge Centre

Mosquito Way-Hatfield, Herts, AL 109SN

United Kingdom

HALAVEN®
(eribulin mesylate) Injection, for intravenous use- 0.5mg/ml, 2 ml
Store at 15° - 25°C (59° - 77°F). DO NOT FREEZE

QTY: 00XXX EXP: MM-YYYY LOT: F1XXYZZZ
(22) 900XXX MMYYYY F1XXYZZZ 7

NDC 43624-002-01

(0X) 50X XXXXX 00X X X0 XXX

Manufactured by : BSP Pharmaceuticals SpA-Latina Scalo, Italy.